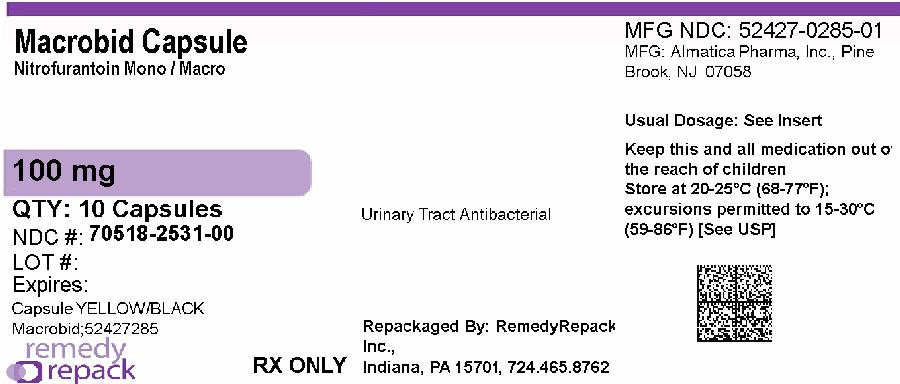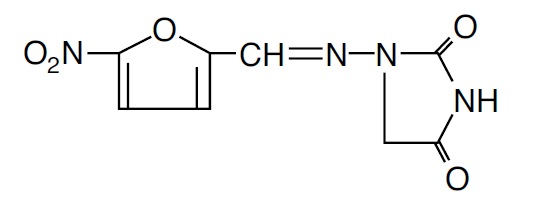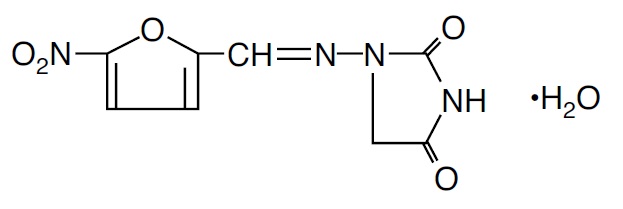 DRUG LABEL: Macrobid
NDC: 70518-2531 | Form: CAPSULE
Manufacturer: REMEDYREPACK INC.
Category: prescription | Type: HUMAN PRESCRIPTION DRUG LABEL
Date: 20260209

ACTIVE INGREDIENTS: NITROFURANTOIN 25 mg/1 1; NITROFURANTOIN MONOHYDRATE 75 mg/1 1
INACTIVE INGREDIENTS: CARBOMER HOMOPOLYMER TYPE B (ALLYL SUCROSE CROSSLINKED); STARCH, CORN; D&C YELLOW NO. 10; FD&C BLUE NO. 1; FD&C RED NO. 40; GELATIN, UNSPECIFIED; LACTOSE, UNSPECIFIED FORM; MAGNESIUM STEARATE; POVIDONE, UNSPECIFIED; TALC; TITANIUM DIOXIDE; SUCROSE

Macrobid (Nitrofurantoin Capsules, USP)(monohydrate/macrocrystals)

To reduce the development of drug-resistant bacteria and maintain the effectiveness of Macrobidand other antibacterial drugs, Macrobidshould be used only to treat or prevent infections that are proven or strongly suspected to be caused by bacteria.

DESCRIPTION

Nitrofurantoin is an antibacterial agent specific for urinary tract infections. Macrobid®(Nitrofurantoin Capsules, USP) (monohydrate/macrocrystals) is a hard gelatin capsule. Each capsule contains 100 mg of nitrofurantoin in the form of 25 mg of nitrofurantoin macrocrystals and 75 mg of nitrofurantoin monohydrate.

The chemical name of nitrofurantoin macrocrystals is 1-[[[5-nitro-2-furanyl]methylene]amino]-2,4-imidazolidinedione. The chemical structure is the following:

Molecular Weight: 238.16

The chemical name of nitrofurantoin monohydrate is 1-[[[5-nitro-2-furanyl]methylene]amino]-2,4- imidazolidinedione monohydrate. The chemical structure is the following:

Molecular Weight: 256.17

Inactive Ingredients:Each capsule contains carbomer 934P, corn starch, compressible sugar, D&C Yellow No. 10, edible gray ink, FD&C Blue No. 1, FD&C Red No. 40, gelatin, lactose, magnesium stearate, povidone, talc, and titanium dioxide.

Meets USP Dissolution Test 8.

CLINICAL PHARMACOLOGY

Each Macrobidcapsule contains two forms of nitrofurantoin. Twenty-five percent is macrocrystalline nitrofurantoin, which has slower dissolution and absorption than nitrofurantoin monohydrate. The remaining 75% is nitrofurantoin monohydrate contained in a powder blend which, upon exposure to gastric and intestinal fluids, forms a gel matrix that releases nitrofurantoin over time. Based on urinary pharmacokinetic data, the extent and rate of urinary excretion of nitrofurantoin from the 100 mg Macrobidcapsule are similar to those of 50 mg or 100 mg Macrodantin® (nitrofurantoin macrocrystals) capsule. Approximately 20% to 25% of a single dose of nitrofurantoin is recovered from the urine unchanged over 24 hours.

Plasma nitrofurantoin concentrations after a single oral dose of the 100 mg Macrobidcapsule are low, with peak levels usually less than 1 mcg/mL. Nitrofurantoin is highly soluble in urine, to which it may impart a brown color. When Macrobidis administered with food, the bioavailability of nitrofurantoin is increased by approximately 40%.

MICROBIOLOGY

Nitrofurantoin is a nitrofuran antimicrobial agent with activity against certain Gram-positive and Gram-negative bacteria.

Mechanism of Action

The mechanism of the antimicrobial action of nitrofurantoin is unusual among antibacterials. Nitrofurantoin is reduced by bacterial flavoproteins to reactive intermediates which inactivate or alter bacterial ribosomal proteins and other macromolecules. As a result of such inactivations, the vital biochemical processes of protein synthesis, aerobic energy metabolism, DNA synthesis, RNA synthesis, and cell wall synthesis are inhibited. Nitrofurantoin is bactericidal in urine at therapeutic doses. The broad-based nature of this mode of action may explain the lack of acquired bacterial resistance to nitrofurantoin, as the necessary multiple and simultaneous mutations of the target macromolecules would likely be lethal to the bacteria.

Interactions with Other Antibiotics

Antagonism has been demonstrated in-vitrobetween nitrofurantoin and quinolone antimicrobials. The clinical significance of this finding is unknown.

Development of resistance to nitrofurantoin has not been a significant problem since its introduction in 1953. Cross-resistance with antibiotics and sulfonamides has not been observed, and transferable resistance is, at most, a very rare phenomenon.

Nitrofurantoin has been shown to be active against most strains of the following bacteria both in-vitroand in clinical infections (see INDICATIONS AND USAGE):

Aerobic and facultative Gram-positive microorganisms:

Staphylococcus saprophyticus

Aerobic and facultative Gram-negative microorganisms:

Escherichia coli

At least 90 percent of the following microorganisms exhibit an in-vitrominimum inhibitory concentration (MIC) less than or equal to the susceptible breakpoint for nitrofurantoin. However, the efficacy of nitrofurantoin in treating clinical infections due to these microorganisms has not been established in adequate and well-controlled trials.

Aerobic and facultative Gram-positive microorganisms:

Coagulase-negative staphylococci (including Staphylococcus epidermidis)

Enterococcusfaecalis

Staphylococcus aureus

Streptococcus agalactiae

Group D streptococci

Viridans group streptococci

Aerobic and facultative Gram-negative microorganisms:

Citrobacter amalonaticus

Citrobacter diversus

Citrobacter freundii

Klebsiella oxytoca

Klebsiella ozaenae

Nitrofurantoin is not active against most strains of Proteusspecies or Serratiaspecies. It has no activity against Pseudomonas species.

Susceptibility Testing:

For specific information regarding susceptibility test interpretive criteria and associated test methods and quality control standards recognized by FDA for this drug, please see: https://www.fda.gov/STIC.

INDICATIONS AND USAGE

Macrobidis indicated only for the treatment of acute uncomplicated urinary tract infections (acute cystitis) caused by susceptible strains of Escherichia colior Staphylococcus saprophyticus.

Nitrofurantoin is not indicated for the treatment of pyelonephritis or perinephric abscesses.

To reduce the development of drug-resistant bacteria and maintain the effectiveness of Macrobidand other antibacterial drugs, Macrobidshould be used only to treat or prevent infections that are proven or strongly suspected to be caused by susceptible bacteria. When culture and susceptibility information are available, they should be considered in selecting or modifying antibacterial therapy. In the absence of such data, local epidemiology and susceptibility patterns may contribute to the empiric selection of therapy.

Nitrofurantoins lack the broader tissue distribution of other therapeutic agents approved for urinary tract infections. Consequently, many patients who are treated with Macrobidare predisposed to persistence or reappearance of bacteriuria. (See CLINICAL STUDIES.)Urine specimens for culture and susceptibility testing should be obtained before and after completion of therapy. If persistence or reappearance of bacteriuria occurs after treatment with Macrobid, other therapeutic agents with broader tissue distribution should be selected. In considering the use of Macrobid, lower eradication rates should be balanced against the increased potential for systemic toxicity and for the development of antimicrobial resistance when agents with broader tissue distribution are utilized.

CONTRAINDICATIONS

Anuria, oliguria, or significant impairment of renal function (creatinine clearance under 60 mL per minute or clinically significant elevated serum creatinine) are contraindications. Treatment of this type of patient carries an increased risk of toxicity because of impaired excretion of the drug.

Because of the possibility of hemolytic anemia due to immature erythrocyte enzyme systems (glutathione instability), the drug is contraindicated in pregnant patients at term (38 to 42 weeks gestation), during labor and delivery, or when the onset of labor is imminent. For the same reason, the drug is contraindicated in neonates under one month of age.

Macrobidis contraindicated in patients with a previous history of cholestatic jaundice/hepatic dysfunction associated with nitrofurantoin.

Macrobidis also contraindicated in those patients with known hypersensitivity to nitrofurantoin.

WARNINGS

Pulmonary reactions:

ACUTE, SUBACUTE, OR CHRONIC PULMONARY REACTIONS HAVE BEEN OBSERVED IN PATIENTS TREATED WITH NITROFURANTOIN. IF THESE REACTIONS OCCUR, MACROBID SHOULD BE DISCONTINUED AND APPROPRIATE MEASURES TAKEN. REPORTS HAVE CITED PULMONARY REACTIONS AS A CONTRIBUTING CAUSE OF DEATH.

CHRONIC PULMONARY REACTIONS (DIFFUSE INTERSTITIAL PNEUMONITIS OR PULMONARY FIBROSIS, OR BOTH) CAN DEVELOP INSIDIOUSLY. THESE REACTIONS OCCUR RARELY AND GENERALLY IN PATIENTS RECEIVING THERAPY FOR SIX MONTHS OR LONGER. CLOSE MONITORING OF THE PULMONARY CONDITION OF PATIENTS RECEIVING LONG-TERM THERAPY IS WARRANTED AND REQUIRES THAT THE BENEFITS OF THERAPY BE WEIGHED AGAINST POTENTIAL RISKS. (SEERESPIRATORY REACTIONS.)

Hepatotoxicity:

Hepatic reactions, including hepatitis, cholestatic jaundice, chronic active hepatitis, and hepatic necrosis, occur rarely. Fatalities have been reported. The onset of chronic active hepatitis may be insidious, and patients should be monitored periodically for changes in biochemical tests that would indicate liver injury. If hepatitis occurs, the drug should be withdrawn immediately and appropriate measures should be taken.

Neuropathy:

Peripheral neuropathy, which may become severe or irreversible, has occurred. Fatalities have been reported. Conditions such as renal impairment (creatinine clearance under 60 mL per minute or clinically significant elevated serum creatinine), anemia, diabetes mellitus, electrolyte imbalance, vitamin B deficiency, and debilitating disease may enhance the occurrence of peripheral neuropathy. Patients receiving long-term therapy should be monitored periodically for changes in renal function.

Optic neuritis has been reported rarely in postmarketing experience with nitrofurantoin formulations.

Hemolytic anemia:

Cases of hemolytic anemia of the primaquine-sensitivity type have been induced by nitrofurantoin. Hemolysis appears to be linked to a glucose-6-phosphate dehydrogenase deficiency in the red blood cells of the affected patients. This deficiency is found in 10 percent of Blacks and a small percentage of ethnic groups of Mediterranean and Near-Eastern origin. Hemolysis is an indication for discontinuing Macrobid; hemolysis ceases when the drug is withdrawn.

Clostridium difficile-associated diarrhea:

Clostridium difficileassociated diarrhea (CDAD) has been reported with use of nearly all antibacterial agents, including nitrofurantoin, and may range in severity from mild diarrhea to fatal colitis. Treatment with antibacterial agents alters the normal flora of the colon leading to overgrowth of C. difficile.

C. difficileproduces toxins A and B which contribute to the development of CDAD. Hypertoxin producing strains of C. difficilecause increased morbidity and mortality, as these infections can be refractory to antimicrobial therapy and may require colectomy. CDAD must be considered in all patients who present with diarrhea following antibiotic use. Careful medical history is necessary since CDAD has been reported to occur over two months after the administration of antibacterial agents.

If CDAD is suspected or confirmed, ongoing antibiotic use not directed against C. difficilemay need to be discontinued. Appropriate fluid and electrolyte management, protein supplementation, antibiotic treatment of C. difficile, and surgical evaluation should be instituted as clinically indicated.

PRECAUTIONS

Information for Patients:

Patients should be advised to take Macrobidwith food (ideally breakfast and dinner) to further enhance tolerance and improve drug absorption. Patients should be instructed to complete the full course of therapy; however, they should be advised to contact their physician if any unusual symptoms occur during therapy.

Patients should be advised not to use antacid preparations containing magnesium trisilicate while taking Macrobid.

Patients should be counseled that antibacterial drugs including Macrobidshould only be used to treat bacterial infections. They do not treat viral infections (e.g., the common cold). When Macrobidis prescribed to treat a bacterial infection, patients should be told that although it is common to feel better early in the course of therapy, the medication should be taken exactly as directed. Skipping doses or not completing the full course of therapy may (1) decrease the effectiveness of the immediate treatment and (2) increase the likelihood that bacteria will develop resistance and will not be treatable by Macrobidor other antibacterial drugs in the future.

Diarrhea is a common problem caused by antibiotics which usually ends when the antibiotic is discontinued. Sometimes after starting treatment with antibiotics, patients can develop watery and bloody stools (with or without stomach cramps and fever) even as late as two or more months after having taken the last dose of the antibiotic. If this occurs, patients should contact their physician as soon as possible.

Repackaged By / Distributed By: RemedyRepack Inc.

625 Kolter Drive, Indiana, PA 15701

(724) 465-8762

General:

Prescribing Macrobidin the absence of a proven or strongly suspected bacterial infection or a prophylactic indication is unlikely to provide benefit to the patient and increases the risk of the development of drug-resistant bacteria.

Drug Interactions:

Antacids containing magnesium trisilicate, when administered concomitantly with nitrofurantoin, reduce both the rate and extent of absorption. The mechanism for this interaction probably is adsorption of nitrofurantoin onto the surface of magnesium trisilicate.

Uricosuric drugs, such as probenecid and sulfinpyrazone, can inhibit renal tubular secretion of nitrofurantoin. The resulting increase in nitrofurantoin serum levels may increase toxicity, and the decreased urinary levels could lessen its efficacy as a urinary tract antibacterial.

Drug/Laboratory Test Interactions:

As a result of the presence of nitrofurantoin, a false-positive reaction for glucose in the urine may occur. This has been observed with Benedict's and Fehling's solutions but not with the glucose enzymatic test.

Carcinogenesis, Mutagenesis, Impairment of Fertility:

Nitrofurantoin was not carcinogenic when fed to female Holtzman rats for 44.5 weeks or to female Sprague-Dawley rats for 75 weeks. Two chronic rodent bioassays utilizing male and female Sprague-Dawley rats and two chronic bioassays in Swiss mice and in BDF1mice revealed no evidence of carcinogenicity.

Nitrofurantoin presented evidence of carcinogenic activity in female B6C3F1mice as shown by increased incidences of tubular adenomas, benign mixed tumors, and granulosa cell tumors of the ovary. In male F344/N rats, there were increased incidences of uncommon kidney tubular cell neoplasms, osteosarcomas of the bone, and neoplasms of the subcutaneous tissue. In one study involving subcutaneous administration of 75 mg/kg nitrofurantoin to pregnant female mice, lung papillary adenomas of unknown significance were observed in the F1 generation.

Nitrofurantoin has been shown to induce point mutations in certain strains of Salmonella typhimuriumand forward mutations in L5178Y mouse lymphoma cells. Nitrofurantoin induced increased numbers of sister chromatid exchanges and chromosomal aberrations in Chinese hamster ovary cells but not in human cells in culture. Results of the sex-linked recessive lethal assay in Drosophila were negative after administration of nitrofurantoin by feeding or by injection. Nitrofurantoin did not induce heritable mutation in the rodent models examined.

The significance of the carcinogenicity and mutagenicity findings relative to the therapeutic use of nitrofurantoin in humans is unknown.

The administration of high doses of nitrofurantoin to rats causes temporary spermatogenic arrest; this is reversible on discontinuing the drug. Doses of 10 mg/kg/day or greater in healthy human males may, in certain unpredictable instances, produce a slight to moderate spermatogenic arrest with a decrease in sperm count.

Pregnancy:

Teratogenic effects:Several reproduction studies have been performed in rabbits and rats at doses up to six times the human dose and have revealed no evidence of impaired fertility or harm to the fetus due to nitrofurantoin. In a single published study conducted in mice at 68 times the human dose (based on mg/kg administered to the dam), growth retardation and a low incidence of minor and common malformations were observed. However, at 25 times the human dose, fetal malformations were not observed; the relevance of these findings to humans is uncertain. There are, however, no adequate and well-controlled studies in pregnant women. Because animal reproduction studies are not always predictive of human response, this drug should be used during pregnancy only if clearly needed.

Non-teratogenic effects:Nitrofurantoin has been shown in one published transplacental carcinogenicity study to induce lung papillary adenomas in the F1 generation mice at doses 19 times the human dose on a mg/kg basis. The relationship of this finding to potential human carcinogenesis is presently unknown. Because of the uncertainty regarding the human implications of these animal data, this drug should be used during pregnancy only if clearly needed.

Labor and Delivery:

See CONTRAINDICATIONS.

Nursing Mothers:

Nitrofurantoin has been detected in human breast milk in trace amounts. Because of the potential for serious adverse reactions from nitrofurantoin in nursing infants under one month of age, a decision should be made whether to discontinue nursing or to discontinue the drug, taking into account the importance of the drug to the mother. (See CONTRAINDICATIONS.)

Pediatric Use:

Macrobidis contraindicated in infants below the age of one month. (See CONTRAINDICATIONS.) Safety and effectiveness in pediatric patients below the age of twelve years have not been established.

Geriatric Use:

Clinical studies of Macrobiddid not include sufficient numbers of subjects aged 65 and over to determine whether they respond differently from younger subjects. Other reported clinical experience has not identified differences in responses between the elderly and younger patients. Spontaneous reports suggest a higher proportion of pulmonary reactions, including fatalities, in elderly patients; these differences appear to be related to the higher proportion of elderly patients receiving long-term nitrofurantoin therapy. As in younger patients, chronic pulmonary reactions generally are observed in patients receiving therapy for six months or longer (see WARNINGS). Spontaneous reports also suggest an increased proportion of severe hepatic reactions, including fatalities, in elderly patients (see WARNINGS).

In general, the greater frequency of decreased hepatic, renal, or cardiac function, and of concomitant disease or other drug therapy in elderly patients should be considered when prescribing Macrobid. This drug is known to be substantially excreted by the kidney, and the risk of toxic reactions to this drug may be greater in patients with impaired renal function. Anuria, oliguria, or significant impairment of renal function (creatinine clearance under 60 mL per minute or clinically significant elevated serum creatinine) are contraindications (see CONTRAINDICATIONS). Because elderly patients are more likely to have decreased renal function, it may be useful to monitor renal function.

ADVERSE REACTIONS

In clinical trials of Macrobid, the most frequent clinical adverse events that were reported as possibly or probably drug-related were nausea (8%), headache (6%), and flatulence (1.5%). Additional clinical adverse events reported as possibly or probably drug-related occurred in less than 1% of patients studied and are listed below within each body system in order of decreasing frequency:

Gastrointestinal:Diarrhea, dyspepsia, abdominal pain, constipation, emesis

Neurologic:Dizziness, drowsiness, amblyopia

Respiratory:Acute pulmonary hypersensitivity reaction (see WARNINGS)

Allergic:Pruritus, urticaria

Dermatologic:Alopecia

Miscellaneous:Fever, chills, malaise

The following additional clinical adverse events have been reported with the use of nitrofurantoin:

Gastrointestinal:Sialadenitis, pancreatitis. There have been sporadic reports of pseudomembranous colitis with the use of nitrofurantoin. The onset of pseudomembranous colitis symptoms may occur during or after antimicrobial treatment. (See WARNINGS.)

Neurologic:Peripheral neuropathy, which may become severe or irreversible, has occurred. Fatalities have been reported. Conditions such as renal impairment (creatinine clearance under 60 mL per minute or clinically significant elevated serum creatinine), anemia, diabetes mellitus, electrolyte imbalance, vitamin B deficiency, and debilitating diseases may increase the possibility of peripheral neuropathy. (See WARNINGS.)

Asthenia, vertigo, and nystagmus also have been reported with the use of nitrofurantoin.

Benign intracranial hypertension (pseudotumor cerebri), confusion, depression, optic neuritis, and psychotic reactions have been reported rarely. Bulging fontanels, as a sign of benign intracranial hypertension in infants, have been reported rarely.

Respiratory:

CHRONIC, SUBACUTE, OR ACUTE PULMONARY HYPERSENSITIVITY REACTIONS MAY OCCUR WITH THE USE OF NITROFURANTOIN.

CHRONIC PULMONARY REACTIONS GENERALLY OCCUR IN PATIENTS WHO HAVE RECEIVED CONTINUOUS TREATMENT FOR SIX MONTHS OR LONGER. MALAISE, DYSPNEA ON EXERTION, COUGH, AND ALTERED PULMONARY FUNCTION ARE COMMON MANIFESTATIONS WHICH CAN OCCUR INSIDIOUSLY. RADIOLOGIC AND HISTOLOGIC FINDINGS OF DIFFUSE INTERSTITIAL PNEUMONITIS OR FIBROSIS, OR BOTH, ARE ALSO COMMON MANIFESTATIONS OF THE CHRONIC PULMONARY REACTION. FEVER IS RARELY PROMINENT.

THE SEVERITY OF CHRONIC PULMONARY REACTIONS AND THEIR DEGREE OF RESOLUTION APPEAR TO BE RELATED TO THE DURATION OF THERAPY AFTER THE FIRST CLINICAL SIGNS APPEAR. PULMONARY FUNCTION MAY BE IMPAIRED PERMANENTLY, EVEN AFTER CESSATION OF THERAPY. THE RISK IS GREATER WHEN CHRONIC PULMONARY REACTIONS ARE NOT RECOGNIZED EARLY.

In subacute pulmonary reactions, fever and eosinophilia occur less often than in the acute form. Upon cessation of therapy, recovery may require several months. If the symptoms are not recognized as being drug-related and nitrofurantoin therapy is not stopped, the symptoms may become more severe.

Acute pulmonary reactions are commonly manifested by fever, chills, cough, chest pain, dyspnea, pulmonary infiltration with consolidation or pleural effusion on x-ray, and eosinophilia. Acute reactions usually occur within the first week of treatment and are reversible with cessation of therapy. Resolution often is dramatic. (See WARNINGS.)

Changes in EKG (e.g., non-specific ST/T wave changes, bundle branch block) have been reported in association with pulmonary reactions.

Cyanosis has been reported rarely.

Hepatic: Hepatic reactions, including hepatitis, cholestatic jaundice, chronic active hepatitis, and hepatic necrosis, occur rarely. (See WARNINGS.)

Allergic: Lupus-like syndrome associated with pulmonary reaction to nitrofurantoin has been reported. Also, angioedema; maculopapular, erythematous, or eczematous eruptions; anaphylaxis; arthralgia; myalgia; drug fever; chills; and vasculitis (sometimes associated with pulmonary reactions) have been reported. Hypersensitivity reactions represent the most frequent spontaneously-reported adverse events in worldwide postmarketing experience with nitrofurantoin formulations.

Dermatologic: Exfoliative dermatitis and erythema multiforme (including Stevens-Johnson syndrome) have been reported rarely.

Hematologic: Cyanosis secondary to methemoglobinemia has been reported rarely.

Miscellaneous: As with other antimicrobial agents, superinfections caused by resistant organisms, e.g., Pseudomonasspecies or Candidaspecies, can occur.

In clinical trials of Macrobid, the most frequent laboratory adverse events (1% to 5%), without regard to drug relationship, were as follows: eosinophilia, increased AST (SGOT), increased ALT (SGPT), decreased hemoglobin, increased serum phosphorus. The following laboratory adverse events also have been reported with the use of nitrofurantoin: glucose-6-phosphate dehydrogenase deficiency anemia (see WARNINGS), agranulocytosis, leukopenia, granulocytopenia, hemolytic anemia, thrombocytopenia, megaloblastic anemia. In most cases, these hematologic abnormalities resolved following cessation of therapy. Aplastic anemia has been reported rarely.

To request medical information or to report SUSPECTED ADVERSE REACTIONS, contact Almatica Pharma LLC at 1-877-447-7979 or FDA at 1-800-FDA-1088 or www.fda.gov/medwatch.

OVERDOSAGE

Occasional incidents of acute overdosage of nitrofurantoin have not resulted in any specific symptoms other than vomiting. Induction of emesis is recommended. There is no specific antidote, but a high fluid intake should be maintained to promote urinary excretion of the drug. Nitrofurantoin is dialyzable.

DOSAGE AND ADMINISTRATION

Macrobidcapsules should be taken with food.

Adults and Pediatric Patients Over 12 Years: One 100 mg capsule every 12 hours for seven days.

HOW SUPPLIED

Macrobid (Nitrofurantoin Capsules, USP) (monohydrate/macrocrystals) is available as 100 mg opaque black and yellow capsules imprinted “(band) Macrobid (band)” on one half and “52427-285” on the other.

NDC: 70518-2531-00

PACKAGING: 10 in 1 BOTTLE PLASTIC

Store at controlled room temperature 15°C to 30°C (59°F to 86°F).

Rx only

Repackaged and Distributed By:

Remedy Repack, Inc.

625 Kolter Dr. Suite #4 Indiana, PA 1-724-465-8762

CLINICAL STUDIES

Controlled clinical trials comparing Macrobid100 mg p.o. q12h and Macrodantin50 mg p.o. q6h in the treatment of acute uncomplicated urinary tract infections demonstrated approximately 75% microbiologic eradication of susceptible pathogens in each treatment group.

Repackaged and Distributed By:

Remedy Repack, Inc.

625 Kolter Dr. Suite #4 Indiana, PA 1-724-465-8762

PACKAGE LABEL

DRUG: Macrobid

GENERIC: Nitrofurantoin Monohydrate/Macrocrystalline

DOSAGE: CAPSULE

ADMINSTRATION: ORAL

NDC: 70518-2531-0

COLOR: yellow

SHAPE: CAPSULE

SCORE: No score

SIZE: 20 mm

IMPRINT: Macrobid;52427285

PACKAGING: 10 in 1 BOTTLE, PLASTIC

ACTIVE INGREDIENT(S):

- NITROFURANTOIN MONOHYDRATE 75mg in 1
- NITROFURANTOIN 25mg in 1

INACTIVE INGREDIENT(S):

- CARBOMER HOMOPOLYMER TYPE B (ALLYL SUCROSE CROSSLINKED)
- STARCH, CORN
- D&C YELLOW NO. 10
- FD&C BLUE NO. 1
- FD&C RED NO. 40
- GELATIN, UNSPECIFIED
- LACTOSE, UNSPECIFIED FORM
- MAGNESIUM STEARATE
- POVIDONE, UNSPECIFIED
- TALC
- TITANIUM DIOXIDE
- SUCROSE